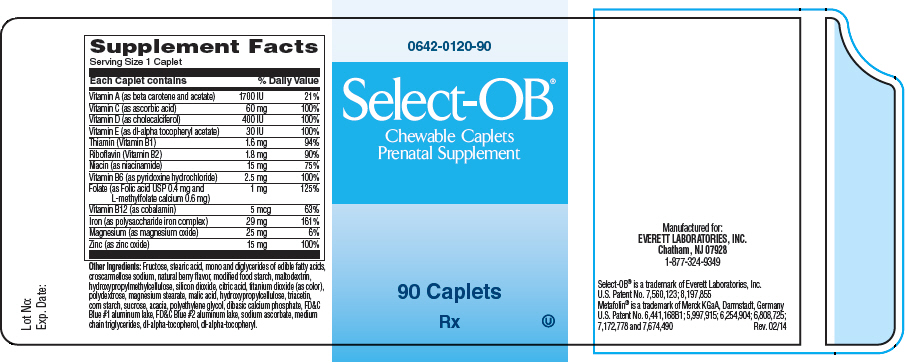 DRUG LABEL: Select OB
NDC: 0642-0120 | Form: TABLET, CHEWABLE
Manufacturer: Everett Laboratories, Inc.
Category: prescription | Type: HUMAN PRESCRIPTION DRUG LABEL
Date: 20140721

ACTIVE INGREDIENTS: .BETA.-CAROTENE 600 [iU]/1 1; VITAMIN A ACETATE 1100 [iU]/1 1; ASCORBIC ACID 60 mg/1 1; CHOLECALCIFEROL 400 [iU]/1 1; .ALPHA.-TOCOPHEROL ACETATE, DL- 30 [iU]/1 1; THIAMINE MONONITRATE 1.6 mg/1 1; RIBOFLAVIN 1.8 mg/1 1; NIACINAMIDE 15 mg/1 1; PYRIDOXINE HYDROCHLORIDE 2.5 mg/1 1; FOLIC ACID 0.4 mg/1 1; LEVOMEFOLATE CALCIUM 0.6 mg/1 1; COBALAMIN 5 ug/1 1; IRON 29 mg/1 1; MAGNESIUM OXIDE 25 mg/1 1; ZINC OXIDE 15 mg/1 1
INACTIVE INGREDIENTS: FRUCTOSE; STEARIC ACID; CROSCARMELLOSE SODIUM; MALTODEXTRIN; HYPROMELLOSES; SILICON DIOXIDE; CITRIC ACID MONOHYDRATE; TITANIUM DIOXIDE; POLYDEXTROSE; MAGNESIUM STEARATE; MALIC ACID; HYDROXYPROPYL CELLULOSE (TYPE H); TRIACETIN; STARCH, CORN; SUCROSE; ACACIA; POLYETHYLENE GLYCOLS; CALCIUM PHOSPHATE, DIBASIC, ANHYDROUS; FD&C BLUE NO. 1; FD&C BLUE NO. 2; SODIUM ASCORBATE; MEDIUM-CHAIN TRIGLYCERIDES; .ALPHA.-TOCOPHEROL, DL-

SELECT-OB® Chewable Caplets
Prenatal Supplement

DESCRIPTION

Supplement Facts
Serving Size 1 Caplet
Each Caplet contains | % Daily Value
Vitamin A (as beta carotene and acetate) | 1700 | IU | 21%
Vitamin C (as ascorbic acid) | 60 | mg | 100%
Vitamin D (as cholecalciferol) | 400 | IU | 100%
Vitamin E (as dl-alpha tocopheryl acetate) | 30 | IU | 100%
Thiamin (Vitamin B1) | 1.6 | mg | 94%
Riboflavin (Vitamin B2) | 1.8 | mg | 90%
Niacin (as niacinamide) | 15 | mg | 75%
Vitamin B6 (as pyridoxine hydrochloride) | 2.5 | mg | 100%
Folate (as Folic acid USP 0.4 mg and L-methylfolate calcium 0.6 mg) | 1 | mg | 125%
Vitamin B12 (as cobalamin) | 5 | mcg | 63%
Iron (as polysaccharide iron complex) | 29 | mg | 161%
Magnesium (as magnesium oxide) | 25 | mg | 6%
Zinc (as zinc oxide) | 15 | mg | 100%

Other Ingredients: Fructose, stearic acid, mono and diglycerides of edible fatty acids, croscarmellose sodium, natural berry flavor, modified food starch, maltodextrin, hydroxypropylmethylcellulose, silicon dioxide, citric acid, titanium dioxide (as color), polydextrose, magnesium stearate, malic acid, hydroxypropylcellulose, triacetin, corn starch, sucrose, acacia, polyethylene glycol, dibasic calcium phosphate, FD&C Blue #1 aluminum lake, FD&C Blue #2 aluminum lake, sodium ascorbate, medium chain triglycerides, dl-alpha-tocopherol, dl-alpha-tocopheryl.

CONTRAINDICATIONS

SELECT-OB® Chewable Caplets are contraindicated in patients with hypersensitivity to any of its components or color additives.

Folic acid is contraindicated in patients with untreated and uncomplicated pernicious anemia, and in those with anaphylactic sensitivity to folic acid.

Iron therapy is contraindicated in patients with hemochromatosis and patients with iron storage disease or the potential for iron storage disease due to chronic hemolytic anemia (e.g., inherited anomalies of hemoglobin structure or synthesis and/or red cell enzyme deficiencies, etc.), pyridoxine responsive anemia, or cirrhosis of the liver.

Cyanocobalamin is contraindicated in patients with sensitivity to cobalt or to cyanocobalamin (vitamin B12).

WARNING

Accidental overdose of iron-containing products is a leading cause of fatal poisoning in children under 6. Keep this product out of reach of children. In case of accidental overdose, call a doctor or a Poison Control Center immediately.

WARNINGS/PRECAUTIONS

Vitamin D supplementation should be used with caution in those with hypercalcemia or conditions that may lead to hypercalcemia such as hyperparathyroidism and those who form calcium-containing kidney stones. High doses of vitamin D can lead to elevated levels of calcium that reside in the blood and soft tissues. Bone pain, high blood pressure, formation of kidney stones, renal failure, and increased risk of heart disease can occur. Prolonged use of iron salts may produce iron storage disease.

Folic acid, especially in doses above 0.1 mg daily, may obscure pernicious anemia, in that hematologic remission may occur while neurological manifestations remain progressive. The use of folic acid doses above 1 mg daily may precipitate or exacerbate the neurological damage of vitamin B12 deficiency.

Avoid overdosage. Keep out of the reach of children.

Drug Interactions

High doses of folic acid may result in decreased serum levels of the anticonvulsant drugs; carbamazepine, fosphenytoin, phenytoin, phenobarbital, valproic acid. Folic acid may decrease a patient's response to methotrexate. Vitamin D supplementation should not be given with large amounts of calcium in those with hypercalcemia or conditions that may lead to hypercalcemia such as hyperparathyroidism and those who form calcium-containing kidney stones. Zinc can inhibit the absorption of certain antibiotics; take at least 2 hours apart to minimize interactions. Consult appropriate references for additional specific vitamin-drug interactions.

Information for Patients

Patients should be counseled to disclose all medical conditions, including use of all medications, vitamins and supplements, pregnancy, and breast-feeding.

ADVERSE REACTIONS

Adverse reactions have been reported with specific vitamins and minerals, but generally at doses substantially higher than those in SELECT-OB® Chewable Caplets. However, allergic and idiosyncratic reactions are possible at any dose. Reported adverse events include skin ailments, gastrointestinal complaints, glucose abnormalities, and visual problems.

HOW SUPPLIED

SELECT-OB® Chewable Caplets are available as a light blue, caplet debossed "EV0120". Available in bottle of 90 and as professional samples.

Rx

USAGE

SELECT-OB® Chewable Caplets provide vitamin and mineral supplementation prior to conception, throughout pregnancy, and during the postnatal period for the lactating and non-lactating mother.

DIRECTIONS FOR USE

Before, during and after pregnancy, chew or swallow one blue SELECT-OB® Chewable Caplet daily, or as directed by a physician.

You should call your doctor for medical advice about serious adverse events. To report a serious adverse event or obtain product information, contact 1-877-324-9349.

KEEP OUT OF REACH OF CHILDREN.

STORAGE AND HANDLING

Store at room temperature, approximately 15°-30°C (59°-86°F), avoid excessive heat, light and moisture.

Manufactured for:
EVERETT LABORATORIES, INC.
Chatham, NJ 07928
1-877-324-9349

PRINCIPAL DISPLAY PANEL - 90 Caplet Bottle Label

0642-0120-90

Select-OB®

Chewable Caplets
Prenatal Supplement

90 Caplets

Rx